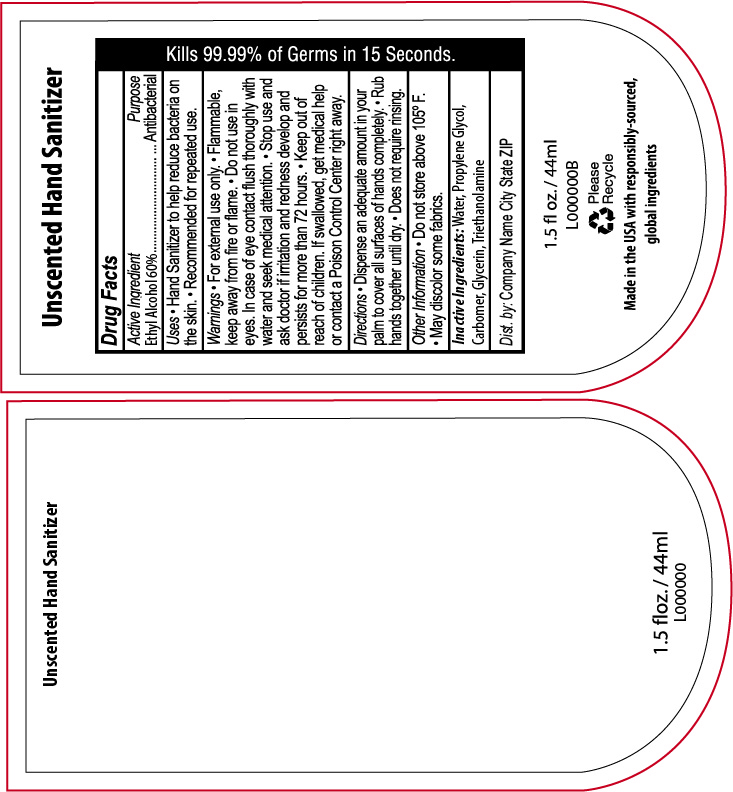 DRUG LABEL: Unscented Hand Sanitizer
NDC: 65692-2074 | Form: GEL
Manufacturer: Raining Rose
Category: otc | Type: HUMAN OTC DRUG LABEL
Date: 20231130

ACTIVE INGREDIENTS: ALCOHOL 60 mL/100 mL
INACTIVE INGREDIENTS: WATER; PROPYLENE GLYCOL; CARBOMER INTERPOLYMER TYPE A (ALLYL SUCROSE CROSSLINKED); GLYCERIN; TROLAMINE

Unscented Hand Sanitizer

Active Ingredient

Ethyl Alcohol 60%

Purpose

Antibacterial

Uses

- Hand Sanitizer to help reduce bacteria on the skin.
- Recommended for repeated use.

Warnings

For external use only.

Flammable, keep away from fire or flame.

Do not use in eyes. In case of eye contact flush thoroughly with water and seek medical attention.

Stop use and ask doctor if irritation and redness develop and persists for more than 72 hours.

Keep out of reach of children. If swallowed, get medical help or contact a Poison Control Center right away.

Directions

- Dispense an adequate amount in your palm to cover all surfaces of hands completely.
- Rub hands together until dry.
- Does not require rinsing.

Other Information

- Do not store above 105 ºF.
- May discolor some fabrics.

Inactive Ingredients

Water, Propylene Glycol, Carbomer, Glycerin, Triethanolamine